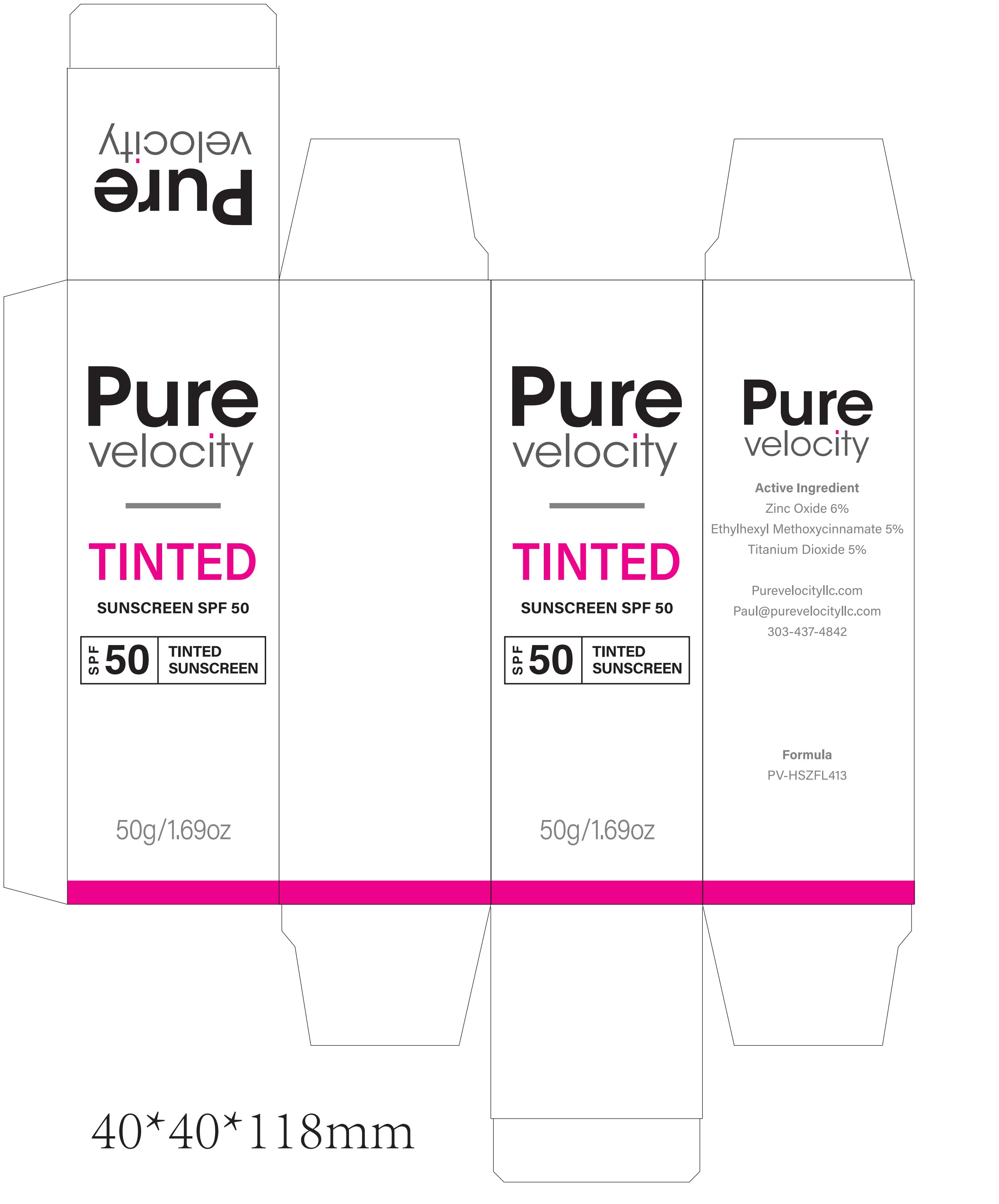 DRUG LABEL: Pure velocity TINTED SUNSCREEN SPF 50
NDC: 60771-0035 | Form: CREAM
Manufacturer: Guangdong Aimu Biological Technology Co., Ltd
Category: otc | Type: HUMAN OTC DRUG LABEL
Date: 20250930

ACTIVE INGREDIENTS: ZINC OXIDE 3 g/100 g; TITANIUM DIOXIDE 2.5 g/100 g
INACTIVE INGREDIENTS: ASCORBIC ACID; SODIUM CHLORIDE; DIMETHICONOL/TRIMETHYLSILOXYSILICATE CROSSPOLYMER (35/65 W/W; 10000000 PA.S); DIPROPYLENE GLYCOL CAPRYLATE; POLYGLYCERYL-2 TRIISOSTEARATE; PHENYL TRIMETHICONE; ABIES PROCERA LEAF; DIMETHICONE/VINYL DIMETHICONE CROSSPOLYMER (HARD PARTICLE); MAGNESIUM STEARATE; DICAPRYLYL CARBONATE; WATER; SIMMONDSIA CHINENSIS (JOJOBA) SEED OIL; DIPALMITOYLPHOSPHATIDYLGLYCEROL, DL-; BENTONITE; ALUMINUM HEXAFLUOROSILICATE; CERAMIDE NP; LIMOSILACTOBACILLUS FERMENTUM

Active Ingredients

ZINC OXIDE
TITANIUM DIOXIDE

Purpose

SUNSCREEN

Uses

If used as directed with other sun protection measures(see Directions)，
decreases the risk of skin cancer and early skin aging caused by the sun.

Warnings

For external use only

Stop Use

Rinse with wate to remove.
Stop use and ask doctor if rash occurs.

Do not use on damaged or broken skin.

When Using

When using this product keep out of eyes.

Keep Out Of Reach Of Children

Dosage & administration

Squeeze out an appropriate amount of Sunscreen and spread evenly on skin.

Inactive ingredients

WATER
GLYCEROL
PROPYLENE GLYCOL
SIMMONDSIA CHINENSIS (JOJOBA) SEED OIL
POLYGLYCERYL-2 TRIISOSTEARATE
PHENYL TRIMETHICONE
DICAPRYLYL CARBONATE
ETHYLHEXYL METHOXYCINNAMATE
TRIMETHYLSILOXYSILICATE
CERA ALBA
DIMETHICONE/VINYL DIMETHICONE CROSSPOLYMER
BENTONITE
SODIUM CHLORIDE
ASCORBIC ACID POLYPEPTIDE
CERAMIDE NP
SPHINGOMONAS FERMENT EXTRACT
SILICA
MAGNESIUM STEARATE
PEG-30 DIPOLYHYDROXYSTEARATE
XANTHAN GUM
SODIUM HYALURONATE
BISABOLOL
TOCOPHEROL
PHENOXYETHANOL
ETHYLHEXYLGLYCERIN
SOLANUM LYCOPERSICUM (TOMATO) FRUIT EXTRACT
TREMELLA FUCIFORMIS (MUSHROOM) EXTRACT
LILIUM CANDIDUM FLOWER EXTRACT
DENDROBIUM NOBILE EXTRACT
STEPHANIA TETRANDRA EXTRACT
TARAXACUM OFFICINALE (DANDELION) LEAF EXTRACT
SAURURUS CHINENSIS LEAF/ROOT EXTRACT
CI 77492
CI 77491
CI 77499
PARFUM